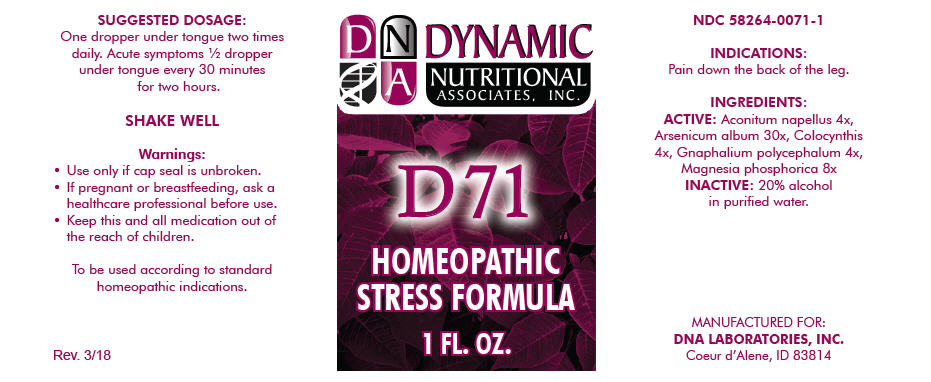 DRUG LABEL: D-71
NDC: 58264-0071 | Form: SOLUTION
Manufacturer: DNA Labs, Inc.
Category: homeopathic | Type: HUMAN OTC DRUG LABEL
Date: 20250113

ACTIVE INGREDIENTS: ACONITUM NAPELLUS 4 [hp_X]/1 mL; ARSENIC TRIOXIDE 30 [hp_X]/1 mL; CITRULLUS COLOCYNTHIS FRUIT PULP 4 [hp_X]/1 mL; PSEUDOGNAPHALIUM OBTUSIFOLIUM 4 [hp_X]/1 mL; MAGNESIUM PHOSPHATE, DIBASIC TRIHYDRATE 8 [hp_X]/1 mL
INACTIVE INGREDIENTS: ALCOHOL; WATER

D-71

NDC 58264-0071-1

INDICATIONS

PURPOSE

Pain down the back of the leg.

INGREDIENTS

ACTIVE

Aconitum napellus 4x, Arsenicum album 30x, Colocynthis 4x, Gnaphalium polycephalum 4x, Magnesia phosphorica 8x

INACTIVE

20% alcohol in purified water.

SUGGESTED DOSAGE

One dropper under tongue two times daily. Acute symptoms ½ dropper under tongue every 30 minutes for two hours.

STORAGE AND HANDLING

SHAKE WELL

Warnings

- Use only if cap seal is unbroken.

PREGNANCY OR BREAST FEEDING

- If pregnant or breastfeeding, ask a healthcare professional before use.

KEEP OUT OF REACH OF CHILDREN

- Keep this and all medication out of the reach of children.

To be used according to standard homeopathic indications.

PRINCIPAL DISPLAY PANEL - 1 FL. OZ. Bottle Label

DYNAMIC
NUTRITIONAL
ASSOCIATES, INC.

D 71

HOMEOPATHIC
STRESS FORMULA

1 FL. OZ.